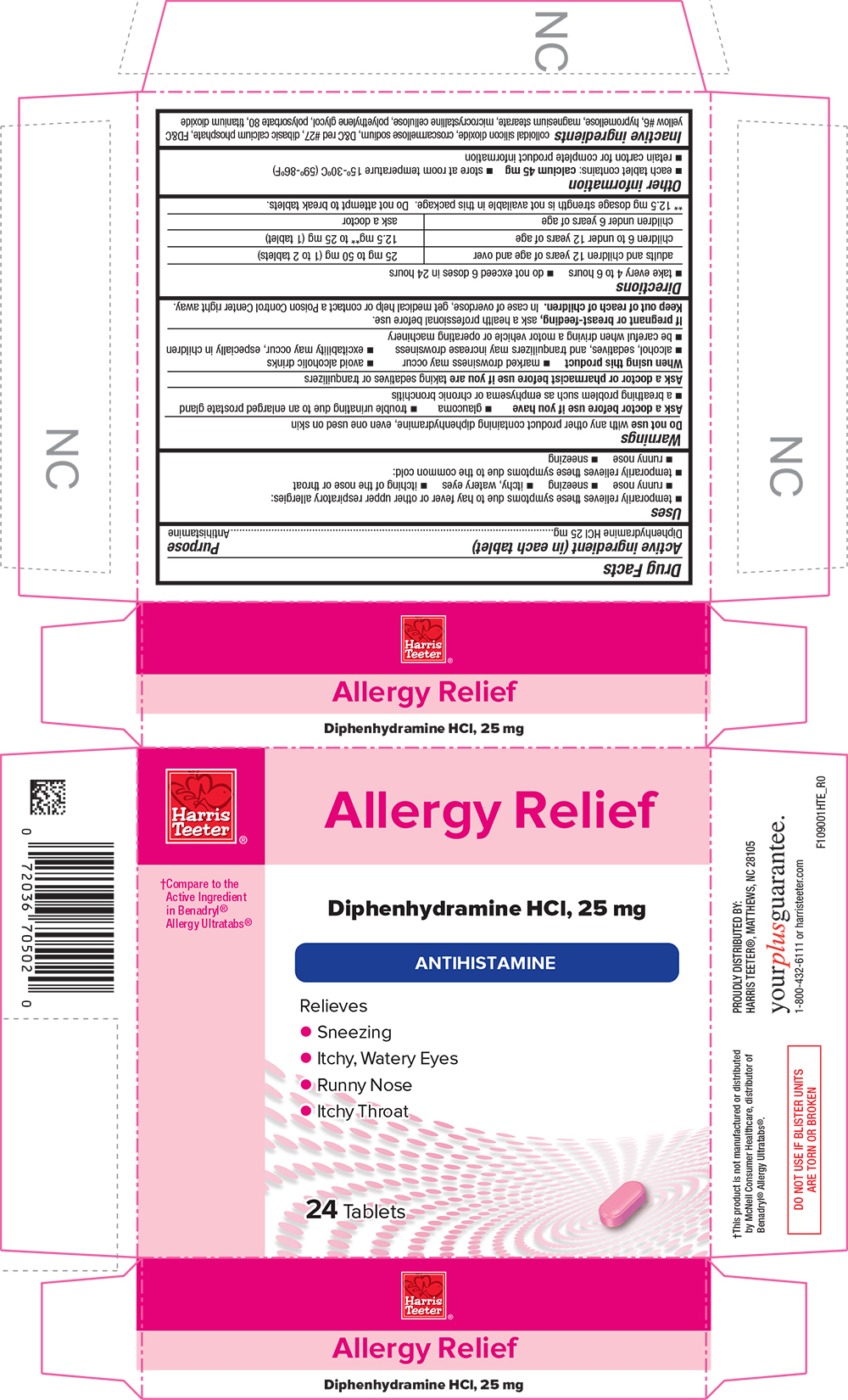 DRUG LABEL: Allergy Relief
NDC: 72036-090 | Form: TABLET, COATED
Manufacturer: Harris Teeter
Category: otc | Type: HUMAN OTC DRUG LABEL
Date: 20251209

ACTIVE INGREDIENTS: DIPHENHYDRAMINE HYDROCHLORIDE 25 mg/1 1
INACTIVE INGREDIENTS: SILICON DIOXIDE; CROSCARMELLOSE SODIUM; D&C RED NO. 27; CALCIUM PHOSPHATE, DIBASIC, ANHYDROUS; FD&C YELLOW NO. 6; HYPROMELLOSE, UNSPECIFIED; MAGNESIUM STEARATE; CELLULOSE, MICROCRYSTALLINE; POLYETHYLENE GLYCOL, UNSPECIFIED; POLYSORBATE 80; TITANIUM DIOXIDE

HTE - 1090 - 2019-1010

Drug Facts

Active ingredient (in each tablet)

Diphenhydramine HCl 25 mg

Purpose

Antihistamine

Uses

- temporarily relieves these symptoms due to hay fever or other upper respiratory allergies:
  - runny nose
  - sneezing
  - itchy, watery eyes
  - itching of the nose or throat
- temporarily relieves these symptoms due to the common cold:
  - runny nose
  - sneezing

Warnings

Do not use with any other product containing diphenhydramine, even one used on skin

Ask a doctor before use if you have

- glaucoma
- trouble urinating due to an enlarged prostate gland
- a breathing problem such as emphysema or chronic bronchitis

Ask a doctor or pharmacist before use if you are taking sedatives or tranquilizers

When using this product

- marked drowsiness may occur
- avoid alcoholic drinks
- alcohol, sedatives, and tranquilizers may increase drowsiness
- excitability may occur, especially in children
- be careful when driving a motor vehicle or operating machinery

PREGNANCY OR BREAST FEEDING

If pregnant or breast-feeding, ask a health professional before use.

Keep out of reach of children. In case of overdose, get medical help or contact a Poison Control Center right away.

Directions

- take every 4 to 6 hours
- do not exceed 6 doses in 24 hours

adults and children 12 years of age and over | 25 mg to 50 mg (1 to 2 tablets)
children 6 to under 12 years of age | 12.5 mg [12.5 mg dosage strength is not available in this package. Do not attempt to break tablets.] to 25 mg (1 tablet)
children under 6 years of age | ask a doctor

Other information

- each tablet contains: calcium 45 mg
- store at room temperature 15°-30°C (59°-86°F)
- retain carton for complete product information

Inactive ingredients

colloidal silicon dioxide, croscarmellose sodium, D&C red #27, dibasic calcium phosphate, FD&C yellow #6, hypromellose, magnesium stearate, microcrystalline cellulose, polyethylene glycol, polysorbate 80, titanium dioxide

PRINCIPAL DISPLAY PANEL

Harris Teeter

Allergy Relief

Compare to the Active Ingredient in Benadryl(R) Allergy Ultratabs(R)

Diphenhydramine HCl, 25 mg

ANTIHISTAMINE

Relieves

Sneezing

Itchy, Watery Eyes

Runny Nose

Itchy Throat

24 Tablets